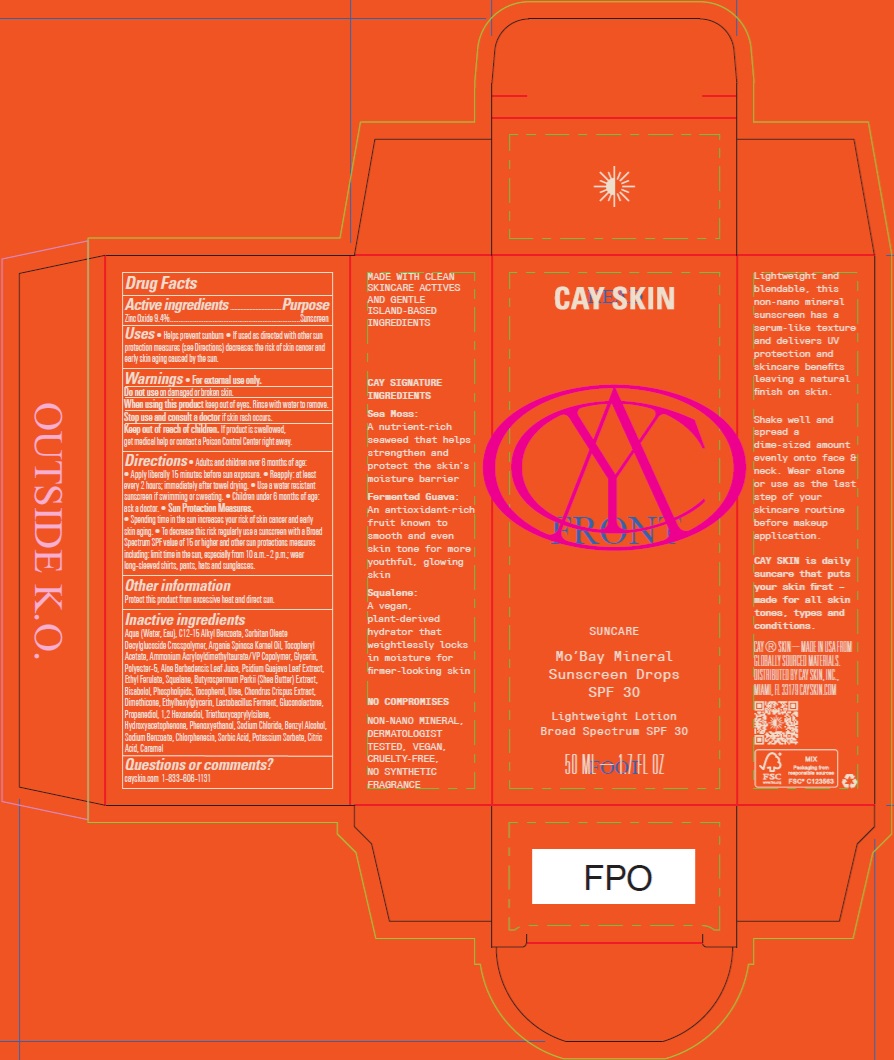 DRUG LABEL: Cay Skin MoBay Mineral Sunscreen Drops SPF 30
NDC: 82657-008 | Form: LOTION
Manufacturer: Cay Skin, Inc.
Category: otc | Type: HUMAN OTC DRUG LABEL
Date: 20241205

ACTIVE INGREDIENTS: ZINC OXIDE 94 mg/1 mL
INACTIVE INGREDIENTS: C12-15 ALKYL BENZOATE; SORBITAN OLEATE DECYLGLUCOSIDE CROSSPOLYMER; AMMONIUM ACRYLOYLDIMETHYLTAURATE/VP COPOLYMER; ETHYL FERULATE; BUTYROSPERMUM PARKII (SHEA) BUTTER EXTRACT; UREA; DIMETHICONE; CHLORPHENESIN; SORBIC ACID; CARAMEL; GLYCERIN; ALOE VERA LEAF; SQUALANE; ETHYLHEXYLGLYCERIN; PROPANEDIOL; TRIETHOXYCAPRYLYLSILANE; POTASSIUM SORBATE; ALPHA-TOCOPHEROL ACETATE; GLUCONOLACTONE; SODIUM CHLORIDE; CITRIC ACID MONOHYDRATE; 1,2-HEXANEDIOL; HYDROXYACETOPHENONE; PSIDIUM GUAJAVA LEAF; CHONDRUS CRISPUS; BENZYL ALCOHOL; WATER; ARGAN OIL; BISABOLOL; OMEGA-3 FATTY ACIDS; TOCOPHEROL; PHENOXYETHANOL; SODIUM BENZOATE

Cay Skin Mo'Bay Mineral Sunscreen Drops SPF 30

Active ingredients

Zinc Oxide 9.4%

Purpose

Sunscreen

Uses

- Helps prevent sunburn
- If used as directed with other sun protection measures (see Directions) decreases the risk of skin cancer and early skin aging caused by the sun.

Warnings

For external use only.

Do not use

on damaged or broken skin.

When using this product

keep out of eyes. Rinse with water to remove.

Stop use and consult a doctor

if skin rash occurs.

Keep out of reach of children.

If product is swallowed, get medical help or contact a Poison Control Center right away.

Directions

- Adults and children over 6 months of age:
- Apply liberally 15 minutes before sun exposure
- Reapply: at least every 2 hours; immediately after towel drying
- Use a water resistant sunscreen if swimming or sweating.
- Children under 6 months of age: ask a doctor
- Sun Protection Measures.
- Spending time in the sun increases your risk of skin cancer and early skin aging.
- To decrease this risk regularly use a sunscreen with a Broad Spectrum SPF value of 15 or higher and other sun protections measures including: limit time in the sun, especially from 10 a.m. - 2 p.m.; wear long-sleeved shirts, pants, hats and sunglasses.

Other information

Protect this product from excessive heat and direct sun.

Inactive ingredients

Aqua (Water, Eau), C12-15 Alkyl Benzoate, Sorbitan Oleate Decylglucoside Crosspolymer, Argania Spinosa Kernel Oil, Tocopheryl Acetate, Ammonium Acryloyldimethyltaurate/VP Copolymer, Glycerin, Polyester-5, Aloe Barbadensis Leaf Juice, Psidium Guajava Leaf Extract, Ethyl Ferulate, Squalane, Butyrospermum Parkii (Shea Butter) Extract, Bisabolol, Phospholipids, Tocopherol, Urea, Chondrus Crispus Extract, Dimethicone, Ethylhexylglycerin, Lactobacillus Ferment, Gluconolactone, Propanediol, 1,2 Hexanediol, Triethoxycaprylylsilane, Hydroxyacetophenone, Phenoxyethanol, Sodium Chloride, Benzyl Alcohol, Sodium Benzoate, Chlorphenesin, Sorbic Acid, Potassium Sorbate, Citric Acid, Caramel

Questions or comments?

cayskin.com 1-833-606-1131

Company Information

DISTRIBUTED BY CAY SKIN, INC.,

MIAMI, FL 33179 CAYSKIN.COM